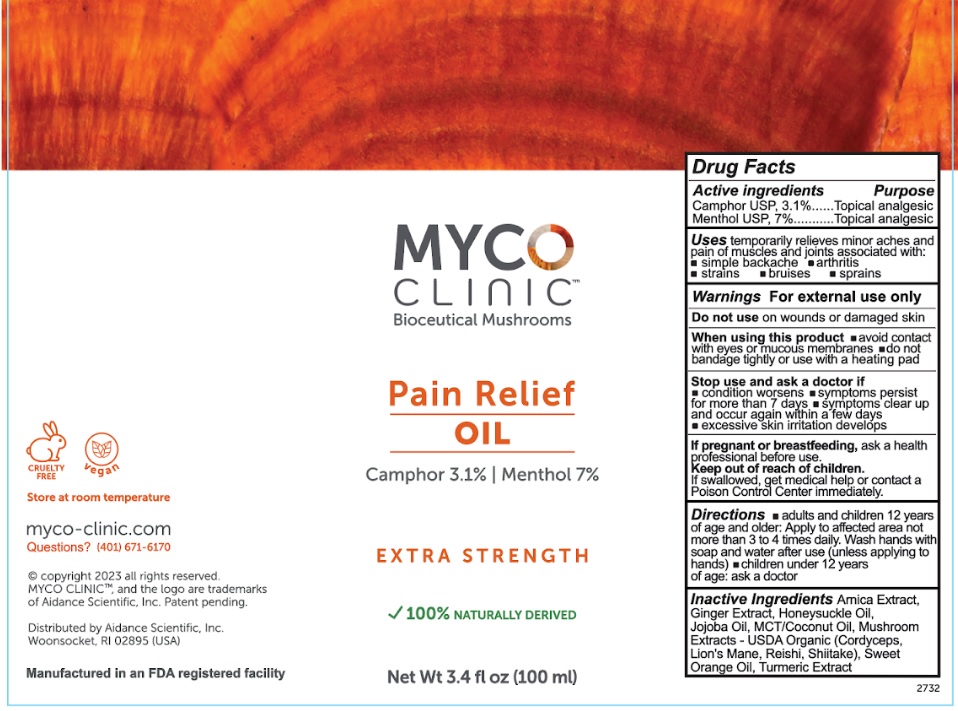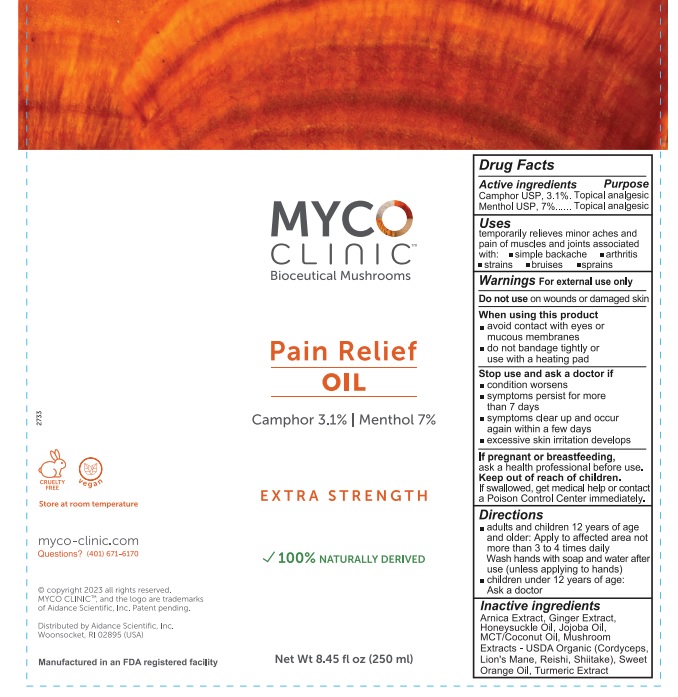 DRUG LABEL: MYCO Clinic Pain Relief
NDC: 24909-011 | Form: OIL
Manufacturer: Aidance Scientific, Inc., DBA Aidance Skincare & Topical Solutions
Category: otc | Type: HUMAN OTC DRUG LABEL
Date: 20241120

ACTIVE INGREDIENTS: CAMPHOR (NATURAL) 3.1 g/100 mL; MENTHOL 7 g/100 mL
INACTIVE INGREDIENTS: ARNICA MONTANA FLOWER; GINGER; AQUILEGIA CANADENSIS WHOLE; JOJOBA OIL; COCONUT OIL; OPHIOCORDYCEPS SINENSIS; REISHI; SHIITAKE MUSHROOM; ORANGE OIL, COLD PRESSED; TURMERIC; HERICIUM ERINACEUS FRUITING BODY

24909-011 MYCO CLINIC Pain Relief Oil
MYCO Clinic Pain Relief Oil

Active Ingredients Purpose

Camphor USP, 3.1%.......Topical analgesic
Menthol USP, 7%.......Topical analgesic

Uses

temporarily relieves minor aches and pain of muscles and joints associated with: simple backache, arthritis, strains, bruises, sprains

Warnings

For external use only

Do not use onwounds or damaged skin

When using this productavoid contact with eyes or mucous membranes - do not bandage tightly or use with a heating pad

Stop use and ask a doctor ifcondition worsens, symptoms persist for more than 7 days, symptoms clear up and occur again within a few days, excessive skin irritation develops

If pregnant or breastfeeding, ask a health professional before use.

Keep out of reach of children. If swallowed, get medical help or contact a Poison Control Center immediately.

Directions

Adults and children 12 years of age and older: Apply to affected area not more than 3 to 4 times daily. Wash hands with soap and water after use (unless applying to hands)
children under 12 years of age: ask a doctor

Inactive Ingredients

Arnica Extract, Ginger Extract, Honeysuckle Oil, Jojoba Oil, MCT/Coconut Oil, Mushroom Extracts - USDA Organic (Cordyceps, Lion's Mane, Reishi, Shiitake), Sweet Orange Oil, Turmeric Extract

Questions?

myco-clinic.com
Questions? 401-671-6170